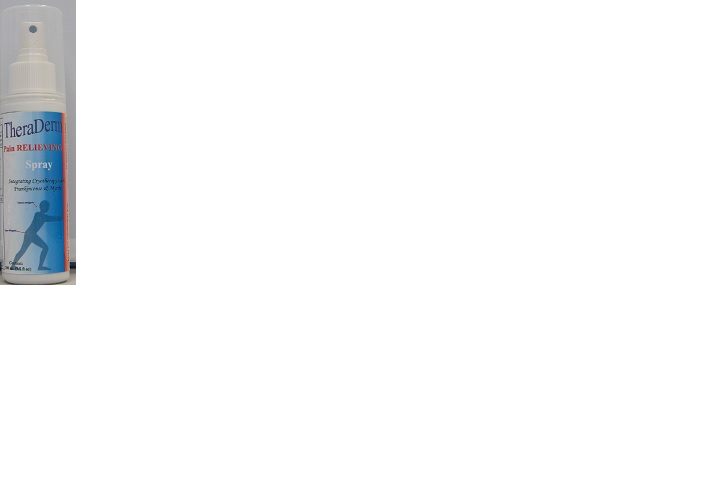 DRUG LABEL: TheraDerm
NDC: 16903-169 | Form: SPRAY
Manufacturer: Manna Omni International Incorporated
Category: otc | Type: HUMAN OTC DRUG LABEL
Date: 20180219

ACTIVE INGREDIENTS: PEPPERMINT OIL 12 mg/120 mg; METHYL SALICYLATE 2-ETHYLBUTYRATE 24 mg/120 mg; MENTHOL 12 mg/120 mg; CAMPHOR OIL 5 mg/120 mg
INACTIVE INGREDIENTS: PRUNUS PERSICA SEED 2 mg/120 mg; (P-HYDROXYPHENYL)DIMETHYLSULFONIUM CHLORIDE 24 mg/120 mg; ALOE VERA LEAF POLYSACCHARIDES 1 mg/120 mg; LIGUSTICUM SINENSE SUBSP. CHUANXIONG ROOT 2 mg/120 mg; FRANKINCENSE OIL 2 mg/120 mg; MYRRH OIL 2 mg/120 mg; GLYCERIN 7 mg/120 mg; COCONUT OIL 1 mg/120 mg; LECITHIN, SOYBEAN 3 mg/120 mg; LAVENDER OIL 1 mg/120 mg; ANGELICA PUBESCENS ROOT 2 mg/120 mg; ZINGIBER CASSUMUNAR ROOT 2 mg/120 mg

Thera Derm Pain Relieving Spray

Warning: For External Use Only.

Use only as directed. Avoid contact with eyes or mucus menmbranes. Do not apply to worn, damaged, or very sensitive skin. Test on a small area before use. Do not Use in combination with other external analgesic products. Do not bandage tightly, or cover with any type of wrap, except clothing. If condition worsens , or persists for more than 7 days, discontinue use and consult a physcian.

Keep out of the reach of Children.

If swallowed, get medical attention or contact poision control Immediately.

INDICATIONS AND USAGE

DIrections: Spray a small amount onto affected area. Repeat 3-4 times daily.

Dosage:

Spray small amount onto affected area every 6 hours no more than 4 times a day.

Other Ingredients:

Aloe Extract, am pelopsis radix extract, bletilla tuber extract, Carthmiflos extract,cimicifugae rhizome extract,echinopsis radix extract, glycerin, glycerrhizae radix extract,kaolin,methyl saliciate, myrrha extract, frankincense extract,Poly Acrylic acid,polysorbate 80,polyvinyl alcohol,propyl glycol,propyl paraben, purified water,rhei rhizome extract,titanium oxide,triethanolamine,glucosamine,and MSM.

Active Ingredients:

Methyl Salcylate, Menthol Natural (From Peppermint oil), and Menthol Crystal Solution.

Purpose:

For the temporary relief of minor arthritis pain, simple back ache, muscle sprains, and muscle strains.

Use:

For the temporary relief of minor muscle pain, simple back aches, muscle strain or sprain.